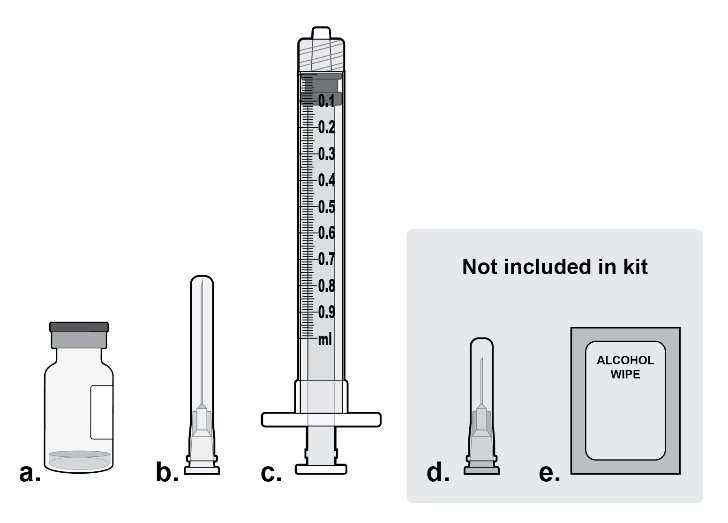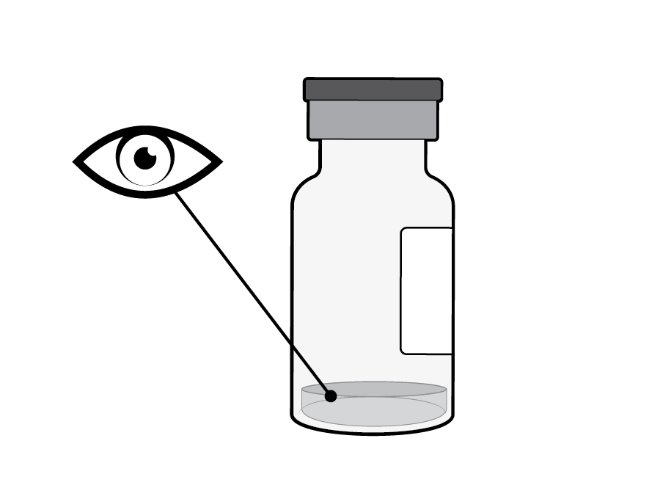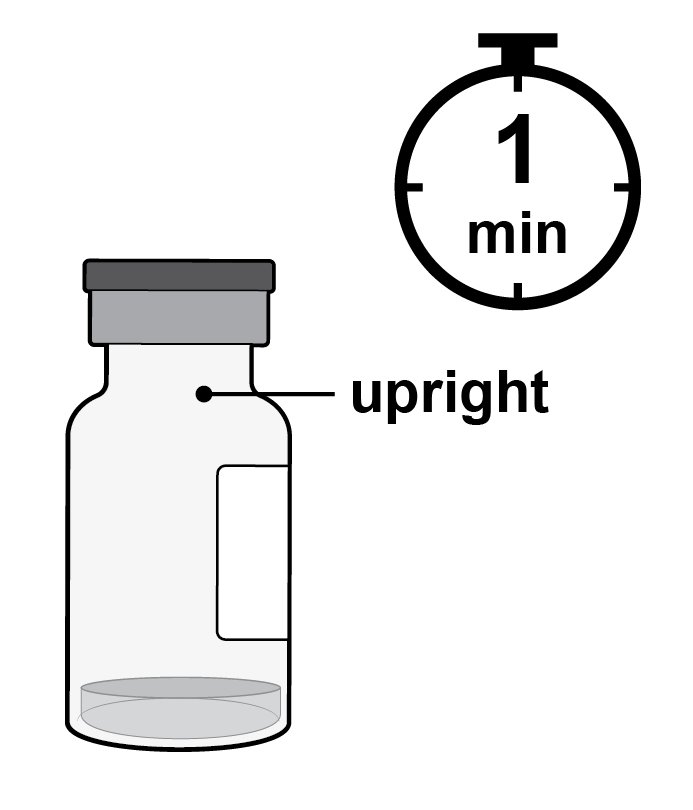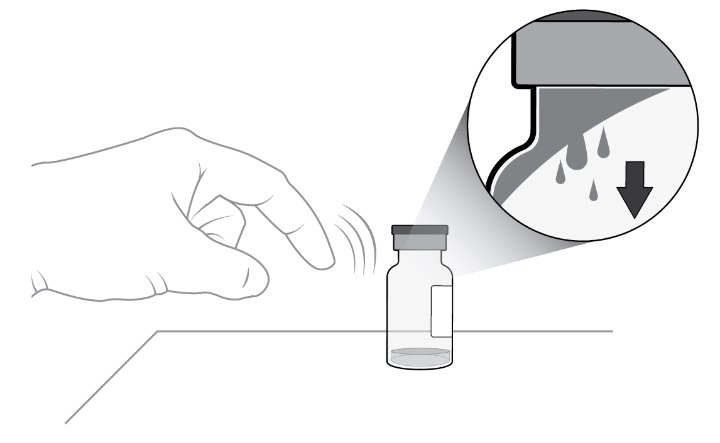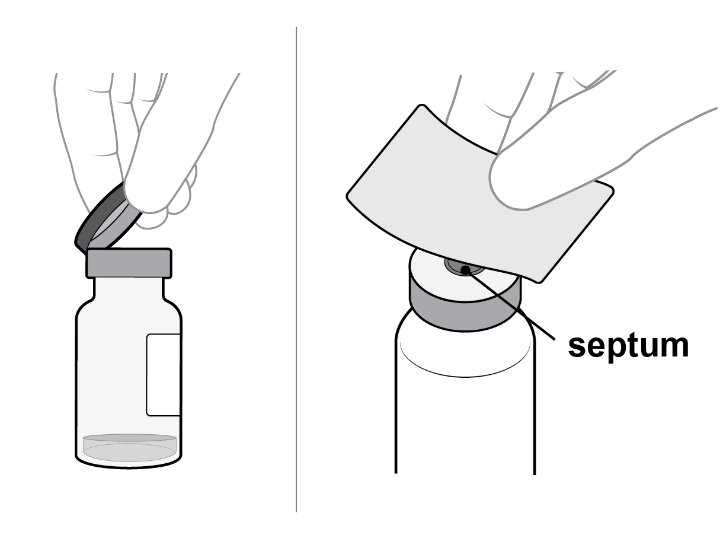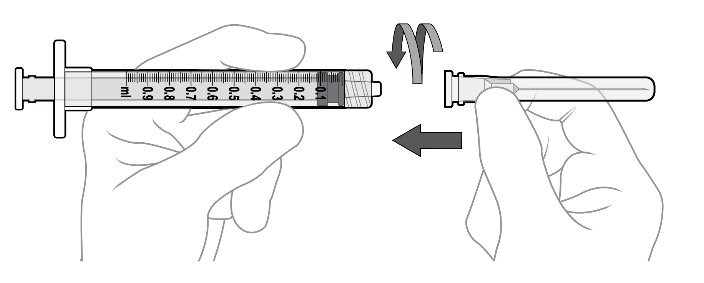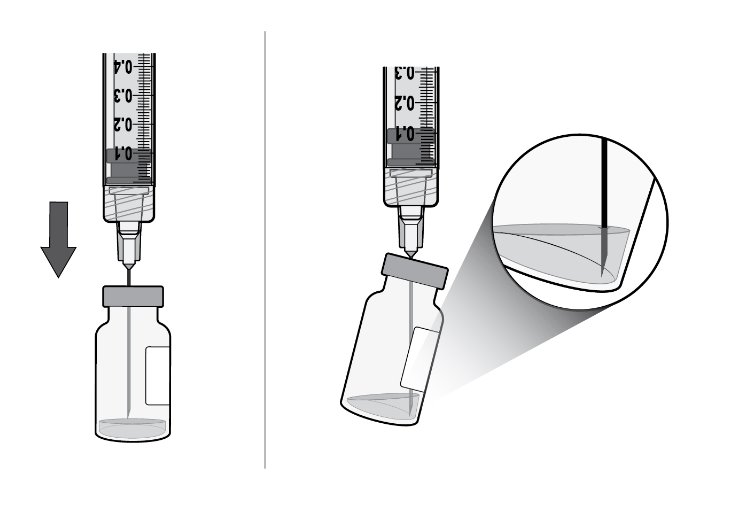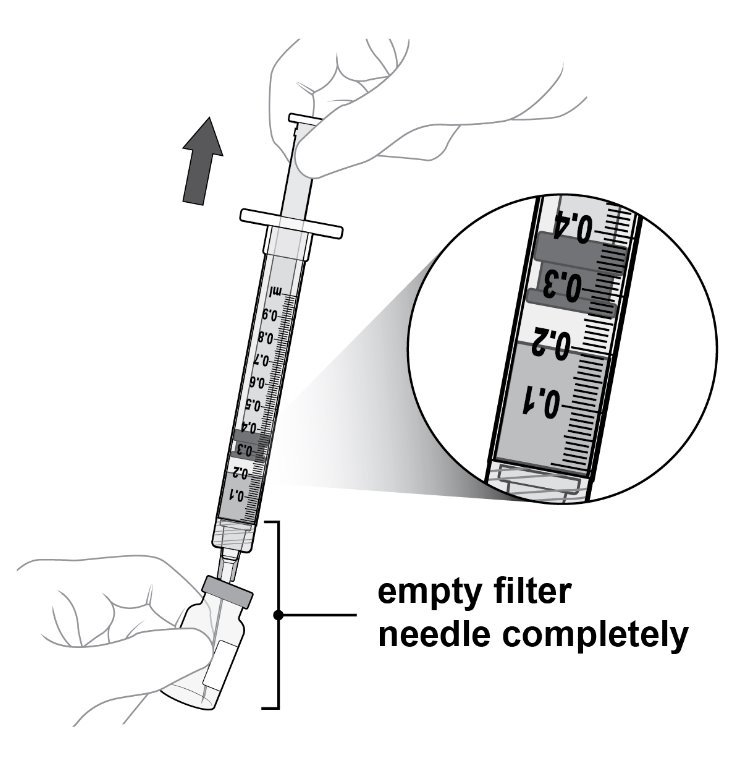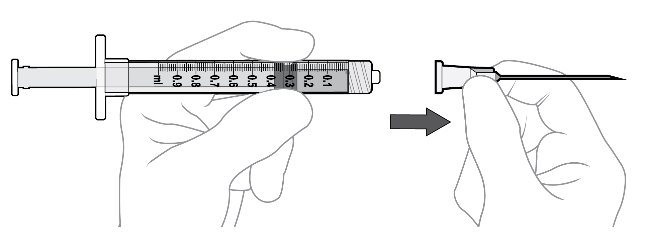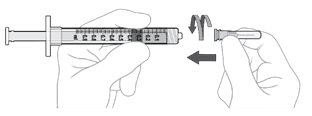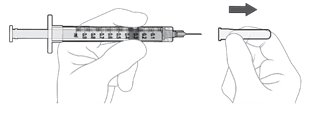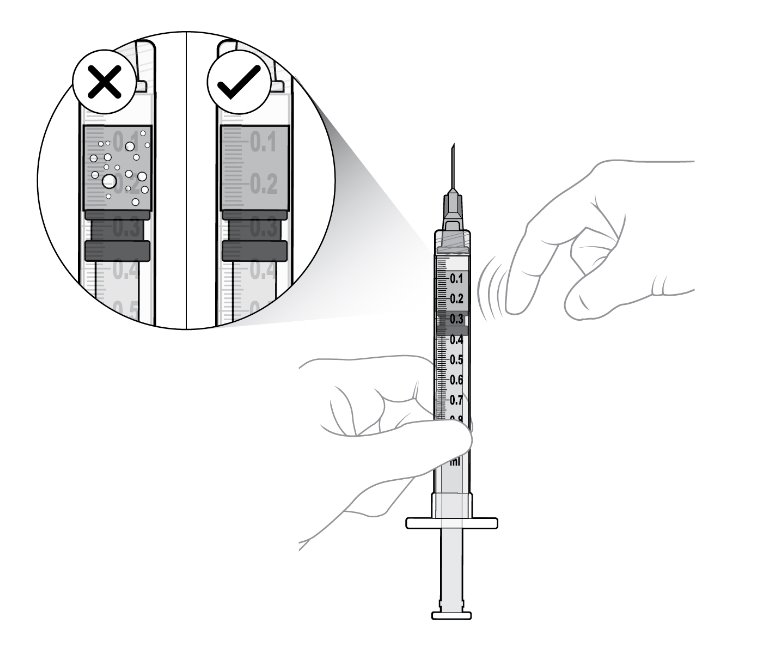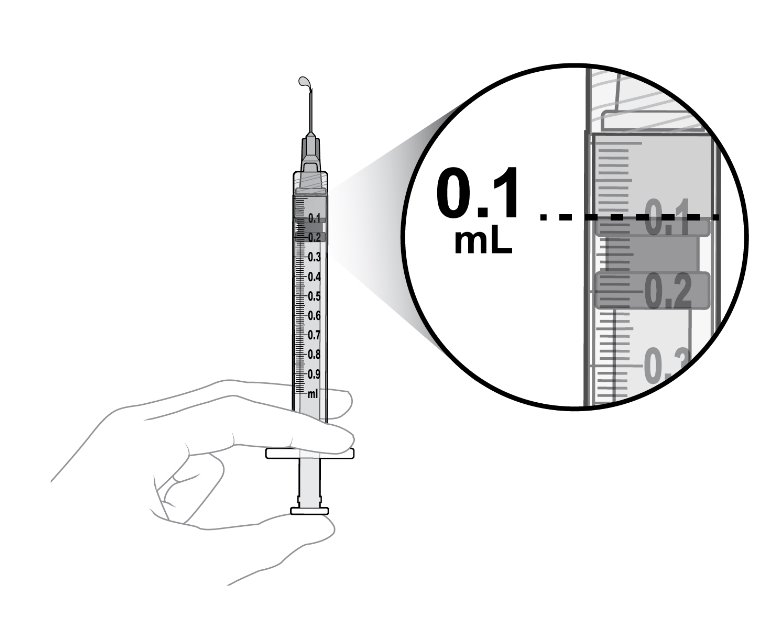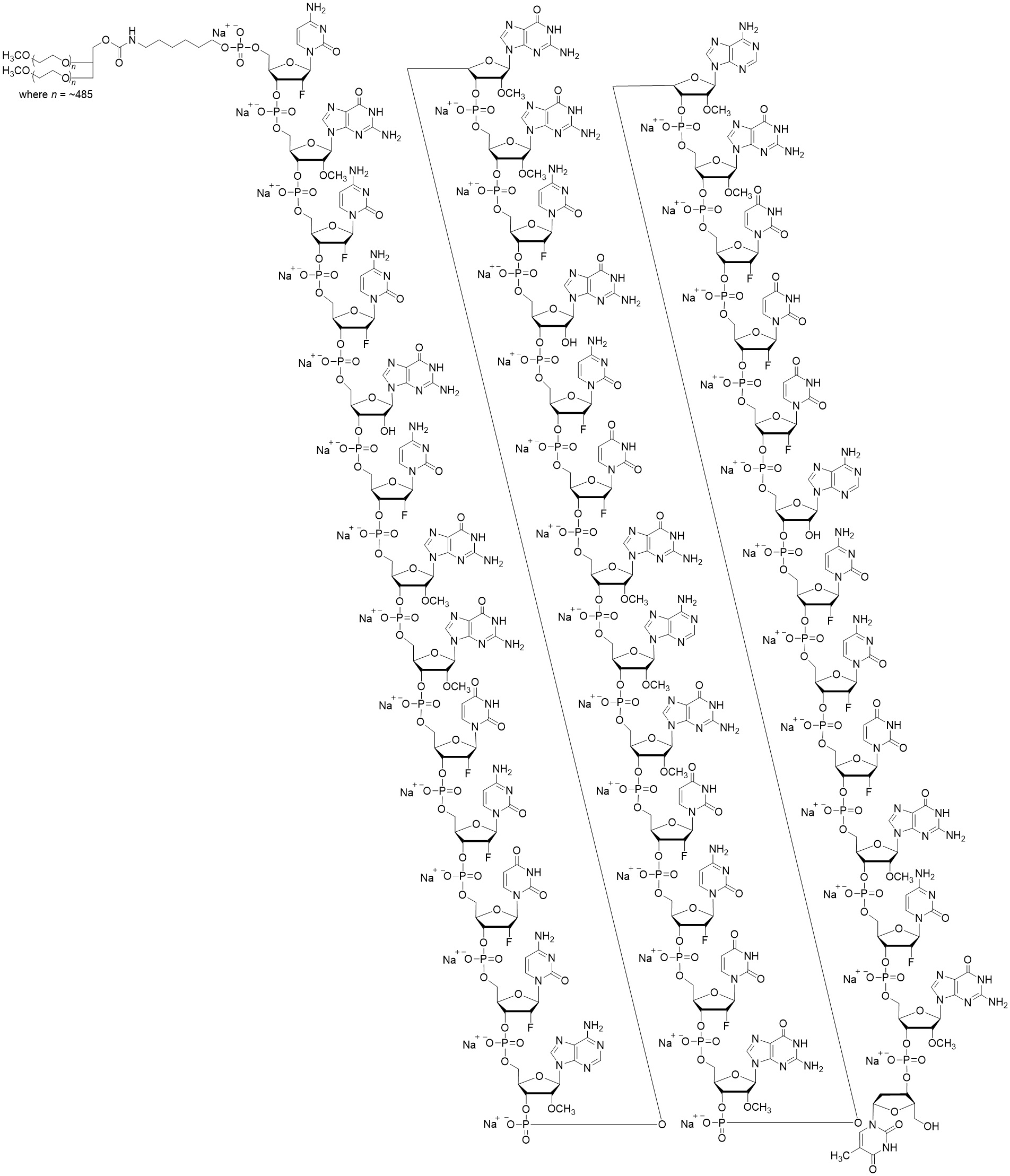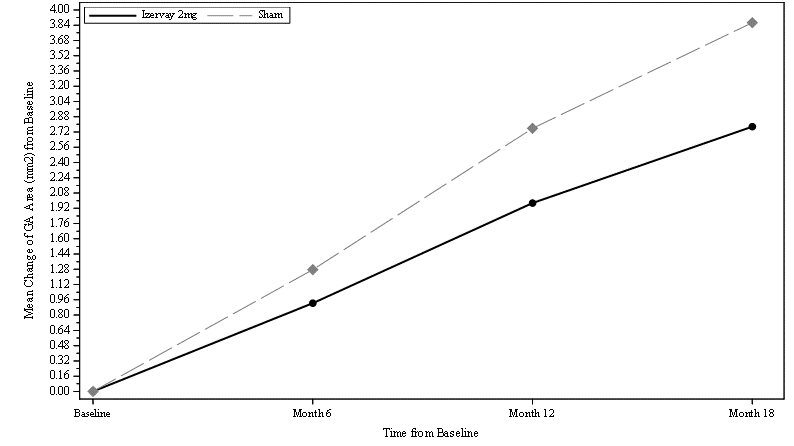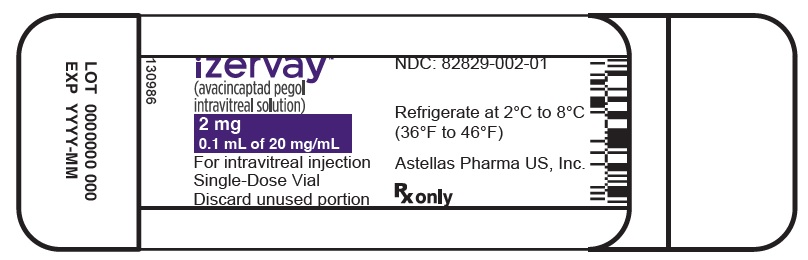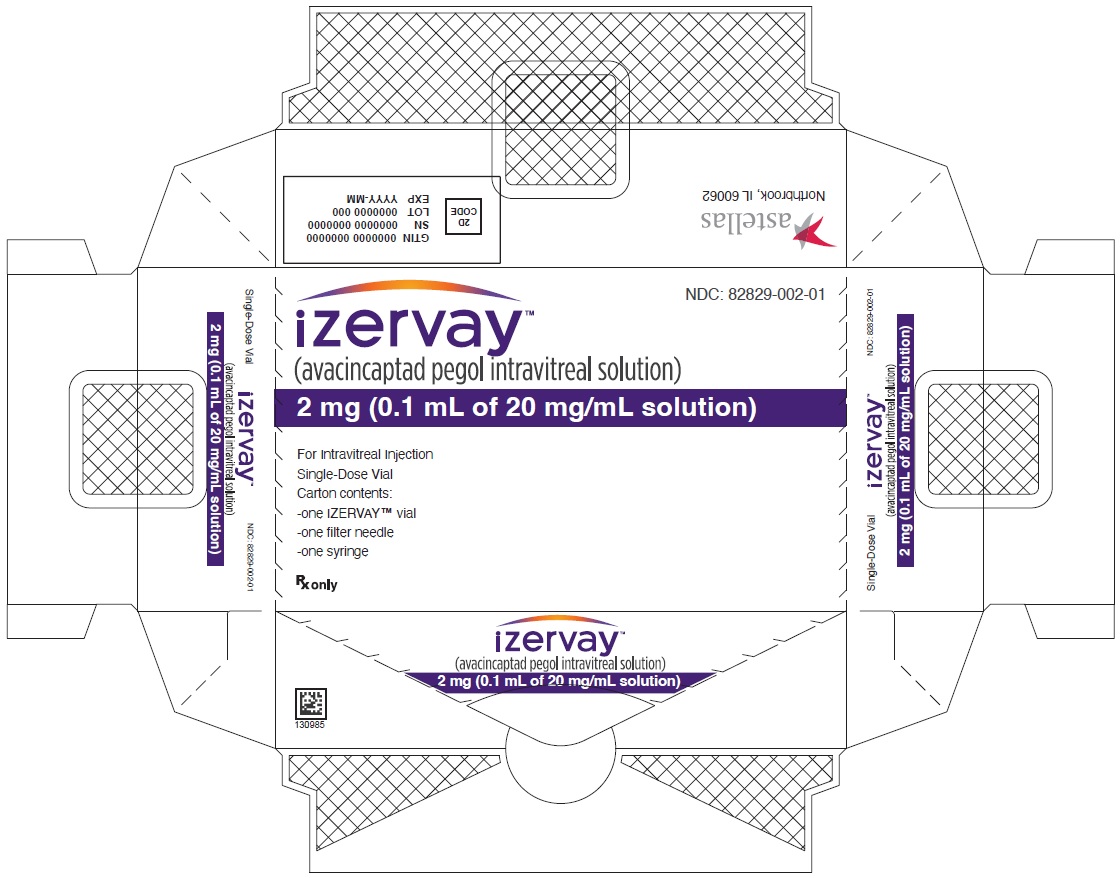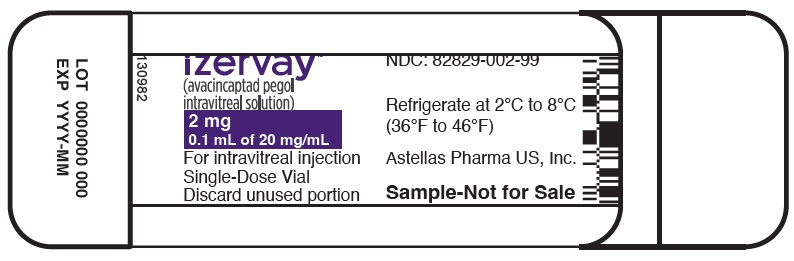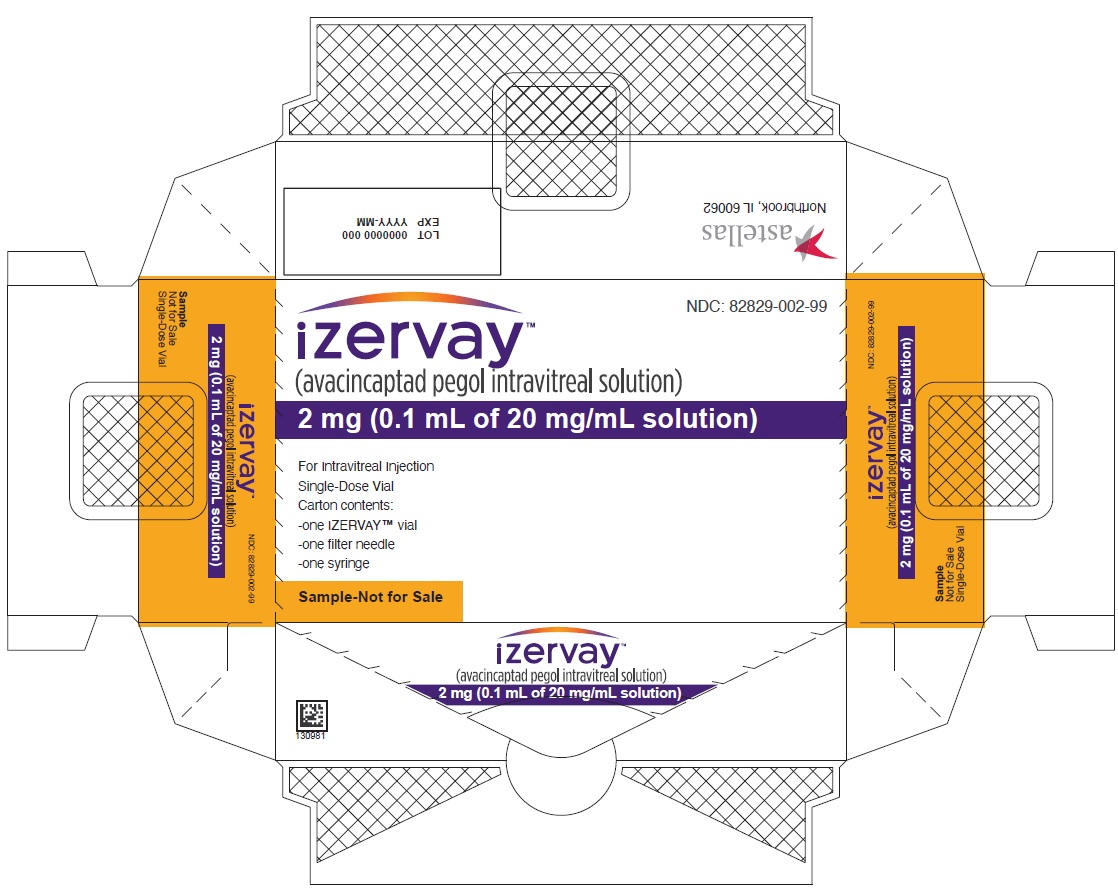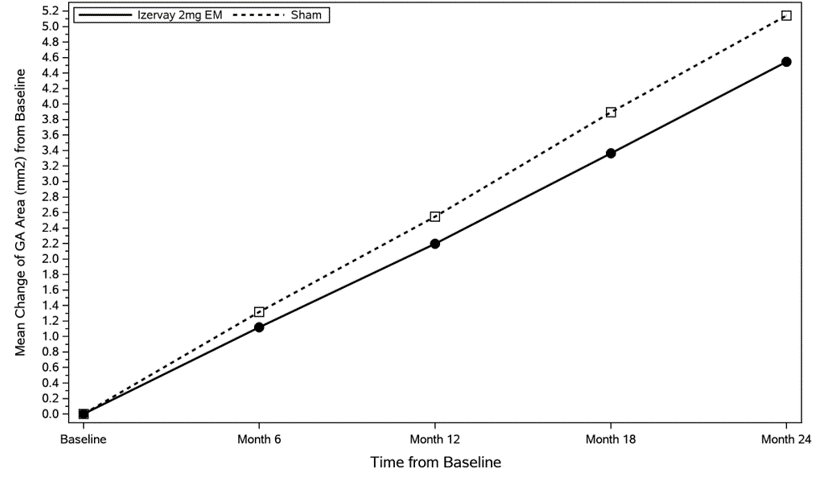 DRUG LABEL: IZERVAY
NDC: 82829-002 | Form: INJECTION
Manufacturer: Astellas Pharma US, Inc.
Category: prescription | Type: HUMAN PRESCRIPTION DRUG LABEL
Date: 20250306

ACTIVE INGREDIENTS: AVACINCAPTAD PEGOL SODIUM 20 mg/1 mL
INACTIVE INGREDIENTS: SODIUM PHOSPHATE, DIBASIC, HEPTAHYDRATE; SODIUM PHOSPHATE, MONOBASIC, MONOHYDRATE; SODIUM CHLORIDE

HIGHLIGHTS OF PRESCRIBING INFORMATION

These highlights do not include all the information needed to use IZERVAY safely and effectively. See full prescribing information for IZERVAY.
IZERVAY™ (avacincaptad pegol intravitreal solution)
Initial U.S. Approval: 2023

RECENT MAJOR CHANGES

Warnings and Precautions, Neovascular AMD (5.2) | 2/2025

1 INDICATIONS AND USAGE

IZERVAY is a complement inhibitor indicated for the treatment of geographic atrophy (GA) secondary to age-related macular degeneration (AMD) (1).

2 DOSAGE AND ADMINISTRATION

The recommended dose for IZERVAY is 2 mg (0.1 mL of 20 mg/mL solution) administered by intravitreal injection to each affected eye once monthly (approximately 28 ± 7 days) (2.2).

3 DOSAGE FORMS AND STRENGTHS

Intravitreal solution: 20 mg/mL in a single-dose vial (3).

4 CONTRAINDICATIONS

- Ocular or periocular infections (4.1).
- Active intraocular inflammation (4.2).

5 WARNINGS AND PRECAUTIONS

- Endophthalmitis and Retinal Detachments (5.1).
- Neovascular AMD (5.2)
- Increase in Intraocular Pressure (IOP) (5.3).

6 ADVERSE REACTIONS

The most common adverse reactions were conjunctival hemorrhage (13%), increased IOP (9%), blurred vision (8%) and neovascular age-related macular degeneration (7%) (6.1).

To report SUSPECTED ADVERSE REACTIONS, contact Astellas Pharma US, Inc. at 1-800-727-7003 or FDA at 1-800-FDA-1088 or www.fda.gov/medwatch.

FULL PRESCRIBING INFORMATION

1 INDICATIONS AND USAGE

IZERVAY™ is indicated for the treatment of geographic atrophy (GA) secondary to age-related macular degeneration (AMD).

2 DOSAGE AND ADMINISTRATION

2.1 General Dosing Information

IZERVAY must be administered by a qualified physician.

2.2 Recommended Dosage

The recommended dose for IZERVAY is 2 mg (0.1 mL of 20 mg/mL solution) administered by intravitreal injection to each affected eye once monthly (approximately every 28 ± 7 days).

2.3 Preparation for Administration

Important information you should know before you begin:

- Read all the instructions carefully before using IZERVAY.
- The IZERVAY kit includes a glass vial, filter needle, and an empty syringe. The glass vial, filter needle, and empty syringe are for single use only.
- Store IZERVAY in the refrigerator at temperatures between 2ºC to 8ºC (36ºF to 46ºF). Do not freeze. Do not shake.
- Prior to use, allow IZERVAY to reach room temperature, 20⁰C to 25⁰C (68⁰F to 77⁰F). The IZERVAY vial may be kept at room temperature for up to 24 hours. Keep the vial in the original carton to protect from light.
- Use aseptic technique to carry out the preparation of the intravitreal injection.
- Each vial should only be used for the treatment of a single eye.

Step 1: Gather Supplies

Gather the following supplies (see Figure A):

a. One IZERVAY vial (included)
b. One sterile 5-micron filter needle 18-gauge x 1½ inch (included)
c. One sterile 1 mL Luer lock syringe with a 0.1 mL dose mark (included)
d. One sterile injection needle 30‑gauge x ½ inch (not included)
NOTE: a 30-gauge injection needle is recommended to avoid increased injection forces that could be experienced with smaller diameter needles.
e. Alcohol swab (not included)

Figure A

Step 2: Inspect Vial

Inspect the liquid in the vial. It should be a clear to slightly opalescent, colorless to slightly yellow liquid solution (see Figure B).

Do not use if particulates, cloudiness, or discoloration are visible.
Do not use if the packaging, vial, filter needle, injection needle, and/or empty syringe are expired, damaged, or have been tampered with.

Figure B

Step 3: Orient Vial

Place the vial upright on a flat surface for about 1 minute after removal from packaging to make sure all liquid settles at the bottom of the vial (see Figure C).

Gently tap the vial with your finger to remove any liquid that may stick to the top of the vial (see Figure D).

Figure C

______________________________________

Figure D

Step 4: Clean Vial

Remove the flip-off cap from the vial (see Figure E).

Gently wipe the vial septum with an alcohol swab (see Figure F).

Figure E Figure F

Step 5: Attach Filter Needle

Using aseptic technique, firmly attach the included 18-gauge x 1½ inch filter needle onto the 1 mL Luer lock syringe and twist clockwise to secure (see Figure G).

Figure G

Step 6: Insert Filter Needle into Vial

Using aseptic technique, push the filter needle all the way into the center of the vial septum (see Figure H).

Tilt the vial slightly so that the needle touches the bottom edge of the vial (see Figure I).

Rotate the filter needle so that the bevel is submerged into the liquid to avoid introduction of air.

Figure H Figure I

Step 7: Withdraw Liquid

Slowly withdraw all the liquid from the vial (see Figure J).

Draw the plunger rod back far enough to completely empty the filter needle.

Figure J

Step 8: Disconnect Filter Needle

Disconnect the filter needle from the syringe and dispose of it in accordance with local regulations (see Figure K).

Do not use the filter needle for the intravitreal injection.

Figure K

Step 9: Attach Injection Needle

Using aseptic technique, firmly attach the 30-gauge x ½ inch injection needle onto the Luer lock syringe. (see Figure L).

Carefully remove the plastic needle shield from the needle by pulling it straight off (see Figure M).

Figure L

________________________________________

Figure M

Step 10: Check Syringe

Check for air bubbles by holding the syringe with the needle pointing up. If there are any air bubbles, gently tap the syringe with your finger until the bubbles rise to the top (see Figure N).

Figure N

Step 11: Prepare Appropriate Dose

Slowly depress the plunger to:

- Expel the air from the syringe
- Align the rubber stopper tip to the 0.1 mL dose mark.

The syringe is now ready for the injection (see Figure O).

Make sure to give the injection immediately after preparing the dose.

Figure O

2.4 Injection Procedure

Only 0.1 mL (2 mg) should be administered to deliver a single dose. Any excess volume should be disposed.

Prior to the intravitreal injection, patients should be monitored for elevated intraocular pressure (IOP) using tonometry [see Warnings and Precautions (5.3)]. If necessary, ocular hypotensive medication can be given to lower the IOP.

The intravitreal injection procedure must be carried out under controlled aseptic conditions, which includes the use of surgical hand disinfection, sterile gloves, a sterile drape, and a sterile eyelid speculum (or equivalent). Adequate anesthesia and a broad-spectrum topical microbicide should be given prior to the injection.

Inject slowly until the rubber stopper reaches the end of the syringe to deliver the volume of 0.1 mL. Confirm delivery of the full dose by checking that the rubber stopper has reached the end of the syringe barrel.

Immediately following the intravitreal injection, patients should be monitored for elevation in intraocular pressure (IOP). Appropriate monitoring may consist of a check for perfusion of the optic nerve head or tonometry.

Following intravitreal injection, patients should be instructed to report any symptoms suggestive of endophthalmitis (e.g., eye pain, redness of the eye, photophobia, blurring of vision) without delay [see Patient Counseling Information (17)].

Each vial and syringe should only be used for the treatment of a single eye. If the contralateral eye requires treatment, a new vial and syringe should be used and the sterile field, syringe, gloves, drapes, eyelid speculum, filter needle, and injection needle should be changed before IZERVAY is administered to the other eye. Repeat the same procedure steps as above.

Any unused medicinal product or waste material should be disposed of in accordance with local regulations.

3 DOSAGE FORMS AND STRENGTHS

Intravitreal solution: 20 mg/mL clear to slightly opalescent, colorless to slightly yellow solution in a single-dose vial.

4 CONTRAINDICATIONS

4.1 Ocular or Periocular Infections

IZERVAY is contraindicated in patients with ocular or periocular infections.

4.2 Active Intraocular Inflammation

IZERVAY is contraindicated in patients with active intraocular inflammation.

5 WARNINGS AND PRECAUTIONS

5.1 Endophthalmitis and Retinal Detachments

Intravitreal injections may be associated with endophthalmitis and retinal detachments [see Adverse Reactions (6.1)]. Proper aseptic injection techniques must always be used when administering IZERVAY in order to minimize the risk of endophthalmitis [see Dosage and Administration (2.4)]. Patients should be instructed to report any symptoms suggestive of endophthalmitis or retinal detachment without delay, to permit prompt and appropriate management [see Patient Counseling Information (17)].

5.2 Neovascular AMD

In the GATHER1 and GATHER2 clinical trials, use of IZERVAY was associated with increased rates of neovascular (wet) AMD or choroidal neovascularization (7% when administered monthly and 4% in the sham group) by Month 12. Over 24 months, the rate of neovascular (wet) AMD or choroidal neovascularization in the GATHER2 trial was 12% in the IZERVAY group and 9% in the sham group. Patients receiving IZERVAY should be monitored for signs of neovascular AMD.

5.3 Increase in Intraocular Pressure

Transient increases in intraocular pressure (IOP) have been observed after an intravitreal injection, including with IZERVAY [see Adverse Reactions (6.1)]. Perfusion of the optic nerve head should be monitored following the injection and managed as needed [see Dosage and Administration (2.4)].

6 ADVERSE REACTIONS

The following potentially serious adverse reactions are described elsewhere in the labeling:

- Ocular and periocular infections [see Contraindications (4.1)]
- Active intraocular inflammation [see Contraindications (4.2)]
- Endophthalmitis and retinal detachments [see Warnings and Precautions (5.1)]
- Neovascular AMD [see Warnings and Precautions (5.2)]
- Increase in intraocular pressure [see Warnings and Precautions (5.3)]

6.1 Clinical Trials Experience

Because clinical trials are conducted under widely varying conditions, adverse reaction rates observed in the clinical trials of a drug cannot be directly compared to rates in the clinical trials of another drug and may not reflect the rates observed in practice.

The safety of avacincaptad pegol was evaluated in 733 patients with AMD in two sham-controlled studies (GATHER1 and GATHER2). Of these patients, 292 were treated with intravitreal IZERVAY 2 mg (0.1 mL of 20 mg/mL solution) [see Clinical Studies (14)]. Three hundred thirty-two (332) patients were assigned to sham.

Adverse reactions reported in ≥2% of patients who received treatment with IZERVAY pooled across GATHER1 and GATHER2, are listed below in Table 1.

Table 1: Common Ocular Adverse Reactions (≥2%) and greater than Sham in Study Eye
Adverse Drug Reactions | IZERVAY N=292 | Sham N=332
Conjunctival hemorrhage | 13% | 9%
Increased IOP | 9% | 1%
Blurred vision^1 | 8% | 5%
Choroidal neovascularization | 7% | 4%
Eye pain | 4% | 3%
Vitreous floaters | 2% | <1%
Blepharitis | 2% | <1%
1. Blurred vision includes visual impairment, vision blurred, visual acuity reduced, visual acuity reduced transiently

8 USE IN SPECIFIC POPULATIONS

8.1 Pregnancy

Risk Summary

There are no adequate and well-controlled studies of IZERVAY administration in pregnant women. The use of IZERVAY may be considered following an assessment of the risks and benefits.

Administration of avacincaptad pegol to pregnant rats and rabbits throughout the period of organogenesis resulted in no evidence of adverse effects to the fetus or pregnant female at intravenous (IV) doses 5.5 times and 3.4 times the human exposure, respectively, based on Area Under the Curve (AUC), following a single 2 mg intravitreal (IVT) dose (see Data).

In the U.S. general population, the estimated background risks of major birth defects and miscarriage in clinically recognized pregnancies is 2-4% and 15%-20%, respectively.

Data

Animal Data

An embryo fetal developmental toxicity study was conducted with pregnant rats. Pregnant rats received daily IV injections of avacincaptad pegol from day 6 to day 17 of gestation at 0.1, 0.4, 1.2 mg/kg/day. No maternal or embryofetal adverse effects were observed at any dose evaluated. An increase in the incidence of a non-adverse skeletal variation, described as short thoracolumbar (ossification site without distal cartilage) supernumerary ribs, was observed at all doses evaluated. The clinical relevance of this finding is unknown. Plasma exposures at the high dose were 5.5 times the human AUC of 999 ng•day/mL (23976 ng•hr/mL) following a single 2 mg IVT dose.

An embryo fetal developmental toxicity study was conducted with pregnant rabbits. Pregnant rabbits received daily IV injections of avacincaptad pegol from day 7 to day 19 of gestation at 0.12, 0.4, 1.2 mg/kg/day. No maternal or embryofetal adverse effects were observed at any dose evaluated. Plasma exposure in pregnant rabbits at the highest dose of 1.2 mg/kg/day was 3.4 times the human AUC of 999 ng•day/mL (23976 ng•hr/mL) following a single 2 mg IVT dose.

8.2 Lactation

Risk Summary

There is no information regarding the presence of avacincaptad pegol in human milk, the effects of the drug on the breastfed infant, or the effects of avacincaptad pegol on milk production. Many drugs are transferred in human milk with the potential for absorption and adverse reactions in the breastfed child.

The developmental and health benefits of breastfeeding should be considered along with the mother’s clinical need for IZERVAY, and any potential adverse effects on the breastfed infant from IZERVAY.

8.4 Pediatric Use

Safety and effectiveness of IZERVAY in pediatric patients have not been established.

8.5 Geriatric Use

Of the total number of patients who received IZERVAY in the two clinical trials, 90% (263/292) were ≥65 years and 61% (178/292) were ≥75 years of age. No significant differences in efficacy or safety of avacincaptad pegol were seen with increasing age in these studies. No dose adjustment is required in patients 65 years and above.

11 DESCRIPTION

IZERVAY contains avacincaptad pegol sodium, a complement C5 inhibitor. Avacincaptad pegol is a ribonucleic acid (RNA) aptamer, covalently bound to an approximately 43-kiloDalton (kDa) branched polyethylene glycol (PEG) molecule.

The molecular formula of avacincaptad pegol (free acid form) is C395H492N142O262P39F21((CH2)2O)n where n~970 and the molecular weight is approximately 56 kDa. The structure of avacincaptad pegol sodium is presented below.

IZERVAY (avacincaptad pegol intravitreal solution) is a sterile, clear to slightly opalescent, colorless to slightly yellowish solution in a single-dose glass vial for intravitreal administration. Each single-dose vial is designed to deliver 0.1 mL of solution containing 2 mg avacincaptad pegol (oligonucleotide basis), 0.198 mg dibasic sodium phosphate heptahydrate, 0.0256 mg monobasic sodium phosphate monohydrate, and 0.83 mg sodium chloride. IZERVAY is formulated in Water for Injection, with a target pH of 7.3. IZERVAY does not contain an anti-microbial preservative.

12 CLINICAL PHARMACOLOGY

12.1 Mechanism of Action

Avacincaptad pegol is an RNA aptamer, a PEGylated oligonucleotide that binds to and inhibits complement protein C5. By inhibiting C5, avacincaptad pegol may prevent its cleavage to C5a and C5b thus decreasing membrane attack complex (MAC) formation.

12.2 Pharmacodynamics

Increased GA area growth is reflective of loss of photoreceptors and AMD disease progression. Reductions in the rate of GA growth were observed across avacincaptad pegol treatment groups in studies GATHER1 and GATHER2.

12.3 Pharmacokinetics

Absorption/Distribution

Following monthly dosing of avacincaptad pegol, at steady‑state maximum avacincaptad pegol plasma concentrations (Cmax) are estimated to occur approximately 3 days post-dose and geometric mean (GeoCV%) free avacincaptad pegol plasma Cmax is estimated to be 347 ng/mL (59.0%) in GA secondary to AMD patients. The AUC0-τ days following monthly dosing is 4726 day∙ng/mL, where tau is 28 days.

In humans, avacincaptad pegol plasma concentrations are predicted to be approximately 1,400-fold lower than vitreal concentrations.

Metabolism/Elimination

Metabolism and elimination of avacincaptad pegol has not been fully characterized. Avacincaptad pegol is expected to be catabolized by endonucleases and exonucleases to oligonucleotides of shorter lengths. The estimated apparent systemic half-life of avacincaptad pegol is approximately 8 days.

Specific Populations

Following repeat monthly intravitreal dose administration of 2 mg avacincaptad pegol, no differences in the systemic pharmacokinetics of avacincaptad pegol were observed based on age, gender, and body weight. No special dosage modification is required for any of the populations that have been studied (e.g., age, gender, and body weight). The effect of severe renal impairment or any degree of hepatic impairment on the pharmacokinetics of avacincaptad pegol is unknown. As significant increases in plasma avacincaptad pegol exposures are not expected with intravitreal route of administration, no dosage adjustment is needed based on renal or hepatic impairment status.

13 NONCLINICAL TOXICOLOGY

13.1 Carcinogenesis, Mutagenesis, and Impairment of Fertility

Carcinogenesis

No studies have been conducted on the carcinogenic potential of avacincaptad pegol.

Mutagenesis

Avacincaptad pegol was negative in in vitro (bacterial reverse mutation assay, chromosomal aberration in mammalian cells) and in vivo (mouse bone marrow micronucleus) assays.

Impairment of Fertility

Studies to evaluate the effect of avacincaptad pegol on male or female fertility in animals have not been performed.

14 CLINICAL STUDIES

The safety and efficacy of IZERVAY were demonstrated in two randomized, multi-center, double-masked, sham-controlled, 18- and 24-month studies (GATHER1-NCT02686658 and GATHER2-NCT04435366, respectively) in patients with GA due to AMD. Patient ages ranged from 51 to 97 years with a mean of 77 years. In total, 292 patients were treated with avacincaptad pegol 2 mg, and 332 patients received sham.

In GATHER1, patients were treated with either IZERVAY or sham monthly for 18 months. In the primary analysis for GATHER1, the mean rate of GA growth (slope) from baseline to Month 12, measured by Fundus Autofluorescence (FAF), was evaluated at 3 time points: baseline, Month 6, and Month 12. Over a 12-month period, there was a statistically significant reduction of the rate of GA growth (0.10 mm/year; p<0.01 with square root transformed data) in patients treated with IZERVAY compared to sham. The observed results are shown in Table 2 and Figure 1 below.

In the 24-month GATHER2 study, patients were treated with IZERVAY or sham monthly for the first 12 months. Patients receiving monthly IZERVAY were re-randomized at Month 12 to receive either IZERVAY monthly (EM) or every other month (EOM). Patients treated with sham in the first 12 months continued monthly sham treatment. At any time during the GATHER2 study, patients that developed choroidal neovascularization were concomitantly treated with anti-VEGF therapy.

In GATHER2 analysis, the mean rate of GA growth (slope) measured by FAF was evaluated at 5 time points: baseline, Month 6, Month 12, Month 18, and Month 24. Over a 12-month period, there was a statistically significant reduction of the rate of GA growth (0.05 mm/year; p<0.01 with square root transformed data) in patients treated with IZERVAY EM compared to sham. The annualized rate of GA growth over 24 months in the monthly arm was 2.23 mm^2/year, resulting in treatment difference versus sham of 0.36 mm^2/year (p = 0.0165). In the treatment arm that included patients who received IZERVAY EM treatment for one year and EOM treatment for the second year, the annualized rate of GA growth was 2.10 mm^2/year. The observed results for EM dosing are shown in Table 2 and Figure 2 below.

In both studies, treatment effects in all pre-specified subgroups (e.g., age, gender, baseline GA disc area) were consistent with the results in the overall population.

Table 2: Efficacy Outcomes of IZERVAY Monthly Dosing Compared to Sham in GATHER1 and GATHER2
Efficacy Endpoint; (MMRM Analysis) | Month 12 |  |  |  | Month 24
Efficacy Endpoint; (MMRM Analysis) | GATHER1 |  | GATHER2 |  | GATHER2
Efficacy Endpoint; (MMRM Analysis) | IZERVAY N=67 | Sham; N=110 | IZERVAY N=225 | Sham; N=222 | IZERVAYc N=96 | Sham; N=203
GA Rate of Growth (mm^2/year) (observed)a | 1.22 | 1.89 | 1.75 | 2.12 | 2.23 | 2.59
Difference (95% CI) (mm^2/year); Difference %b; p value | 0.67 (0.21-1.13); 35%; <0.01 |  | 0.38 (0.12-0.63); 18%; <0.01 |  | 0.36 (0.07 – 0.66); 14%; 0.0165
a = non-transformed GA growth slope analysis
b = % difference is calculated by 100*(difference)/(least squares mean from Sham)
c = IZERVAY EM (IZERVAY monthly in both year 1 and year 2)
MMRM= Mixed Models for Repeated Measures

Figure 1: Mean Change in GA Area (mm^2) From Baseline in GATHER1 (Observed data)

Figure 2: Mean Change in GA Area (mm^2) From Baseline in GATHER2 (Observed data)

EM: monthly

16 HOW SUPPLIED/STORAGE AND HANDLING

16.1 How Supplied

IZERVAY (avacincaptad pegol intravitreal solution) is supplied as a sterile, clear to slightly opalescent, colorless to slightly yellowish 20 mg/mL solution in a single-dose glass vial. Each glass vial contains an overfill amount to allow administration of a single 0.1 mL dose of solution containing 2 mg of avacincaptad pegol (oligonucleotide basis). Each IZERVAY carton (NDC 82829-002-01) contains one glass vial, one sterile 5-micron transfer filter needle (18-gauge x 1½ inch, 1.2 mm x 40 mm), and one sterile 1 mL Luer lock syringe.

16.2 Storage and Handling

Store IZERVAY in the refrigerator between 2°C to 8°C (36°F to 46°F). Do not freeze. Do not shake. Keep the vial in the original carton to protect from light.

Prior to use, the unopened glass vial of IZERVAY may be kept at room temperature, 20°C to 25°C (68°F to 77°F), for up to 24 hours. Ensure that the injection is given immediately after preparation of the dose.

17 PATIENT COUNSELING INFORMATION

Advise patients that following IZERVAY administration, patients are at risk of developing neovascular AMD, endophthalmitis, elevated intraocular pressure and retinal detachments. If the eye becomes red, sensitive to light, painful, or if a patient develops a change in vision, instruct the patient to seek immediate care from an ophthalmologist [see Warnings and Precautions (5.1, 5.2)].

Patients may experience temporary visual disturbances and blurring after an intravitreal injection with IZERVAY and the associated eye examinations [see Adverse Reactions (6.1)]. Advise patients not to drive or use machinery until visual function has recovered sufficiently.

IZERVAY™ (avacincaptad pegol intravitreal solution)

Distributed by:

Astellas Pharma US, Inc.

Northbrook, IL 60062

PRINCIPAL DISPLAY PANEL

NDC: 82829-002-01

izervay™
(avacincaptad pegol
intravitreal solution)

2 mg
0.1 mL of 20 mg/mL

For intravitreal injection

Single-Dose Vial

Discard unused portion

Refrigerate at 2°C to 8°C
(36°F to 46°F)

Astellas Pharma US, Inc.

Rx only

PRINCIPAL DISPLAY PANEL

NDC: 82829-002-01

izervay™
(avacincaptad pegol intravitreal solution)

2 mg (0.1 mL of 20 mg/mL solution)

For Intravitreal Injection

Single-Dose Vial

Carton contents:

-one IZERVAY™ vial

-one filter needle

-one syringe

Rx only

PRINCIPAL DISPLAY PANEL

NDC: 82829-002-99

izervay™
(avacincaptad pegol
intravitreal solution)

2 mg
0.1 mL of 20 mg/mL

For intravitreal injection

Single-Dose Vial

Discard unused portion

Refrigerate at 2°C to 8°C
(36°F to 46°F)

Astellas Pharma US, Inc.

Sample-Not for Sale

PRINCIPAL DISPLAY PANEL

NDC: 82829-002-99

izervay™
(avacincaptad pegol intravitreal solution)

2 mg (0.1 mL of 20 mg/mL solution)

For Intravitreal Injection

Single-Dose Vial

Carton contents:

-one IZERVAY™ vial

-one filter needle

-one syringe

Sample-Not for Sale